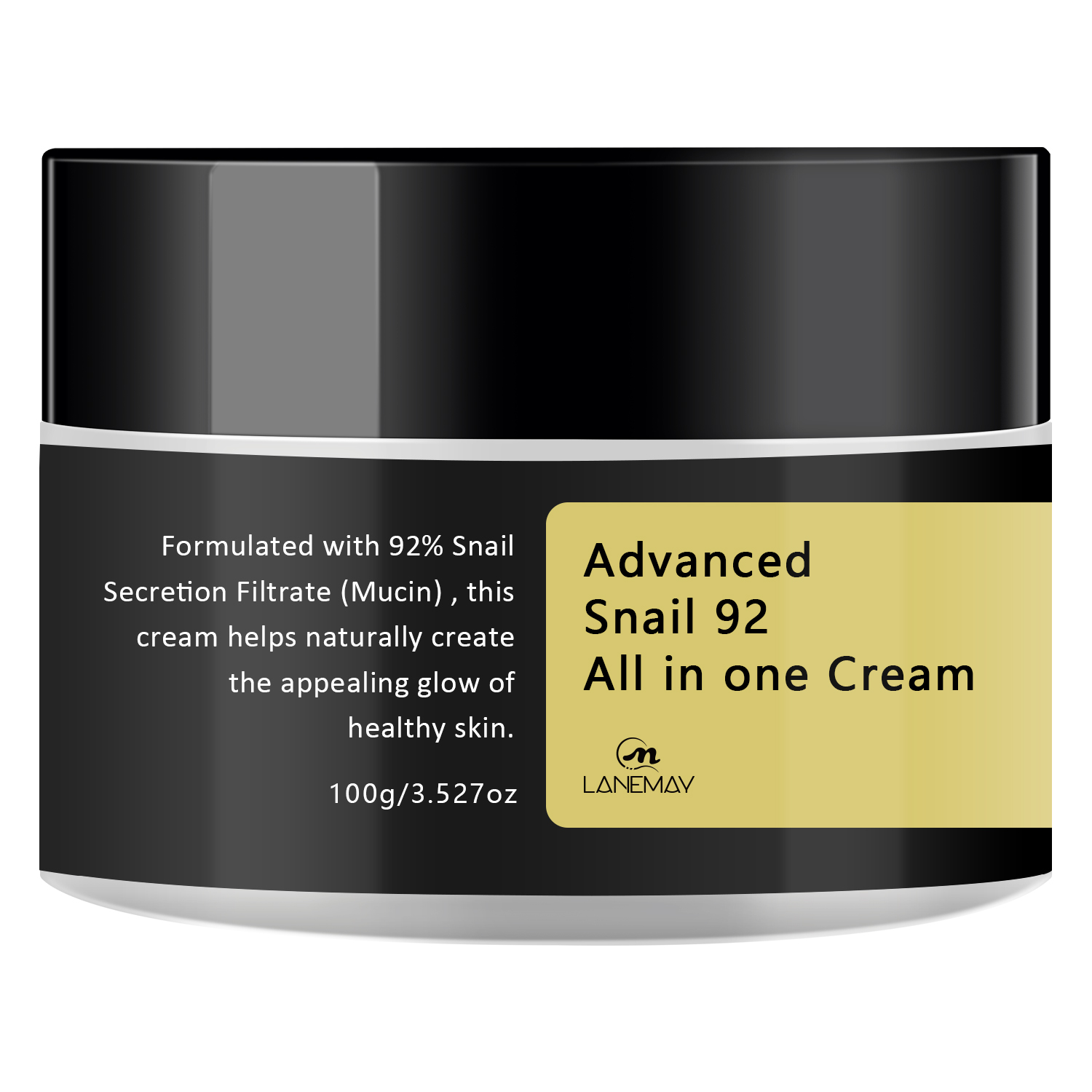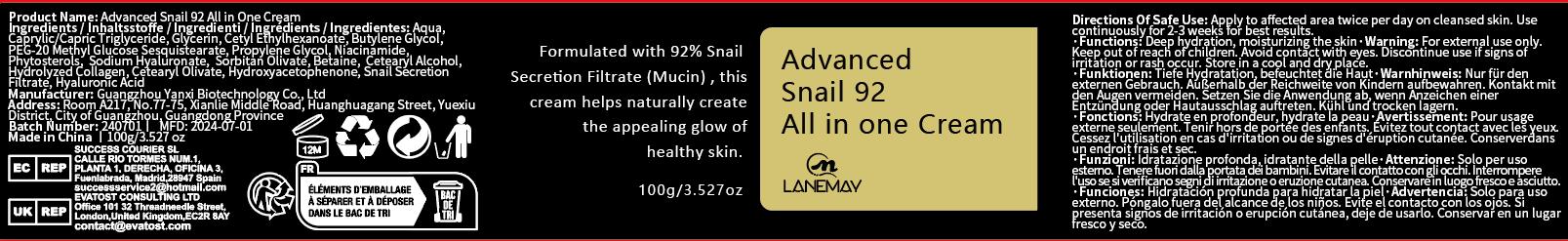 DRUG LABEL: Advanced Snail 92 All in One Cream
NDC: 84025-195 | Form: CREAM
Manufacturer: Guangzhou Yanxi Biotechnology Co., Ltd
Category: otc | Type: HUMAN OTC DRUG LABEL
Date: 20240929

ACTIVE INGREDIENTS: GLYCERIN 5 mg/100 mL; CETYL ETHYLHEXANOATE 3 mg/100 mL
INACTIVE INGREDIENTS: WATER

DOSAGE AND ADMINISTRATION

use as normal face cream

WARNINGS

keep out of children

INACTIVE INGREDIENT

Aqua

INDICATIONS AND USAGE

For face care

keep out of children

PURPOSE

Moisturize the skin